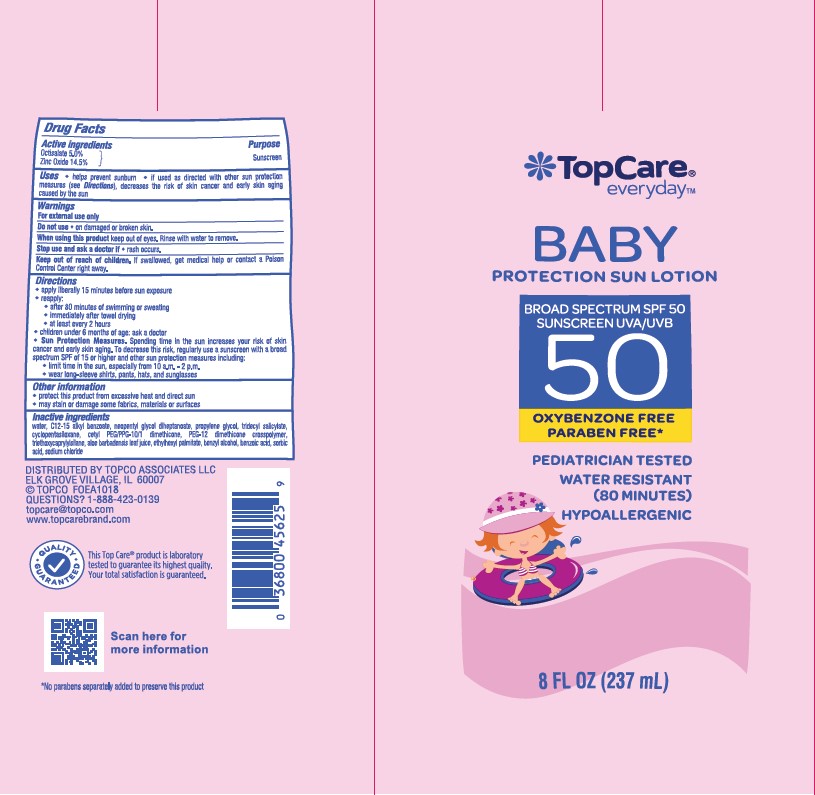 DRUG LABEL: TOPCO TOPCARE EVERYDAY BABY PROTECTION SUN SPF 50
NDC: 36800-347 | Form: LOTION
Manufacturer: TOPCO ASSOCIATES LLC
Category: otc | Type: HUMAN OTC DRUG LABEL
Date: 20241015

ACTIVE INGREDIENTS: ZINC OXIDE 145 mg/1 mL; OCTISALATE 50 mg/1 mL
INACTIVE INGREDIENTS: WATER; NEOPENTYL GLYCOL DIHEPTANOATE; CETYL PEG/PPG-10/1 DIMETHICONE (HLB 5); PROPYLENE GLYCOL; ALOE VERA LEAF; SODIUM CHLORIDE; CYCLOMETHICONE 4; ALKYL (C12-15) BENZOATE; CYCLOMETHICONE 5; BENZYL ALCOHOL; BENZOIC ACID; SORBIC ACID; TRIETHOXYCAPRYLYLSILANE; TRIDECYL SALICYLATE; ETHYLHEXYL PALMITATE

TOPCO TOPCARE EVERYDAY BABY PROTECTION SUN LOTION SPF 50

Active ingredients

Octisalate 5.0%, Zinc Oxide 14.5%

Purpose

Sunscreen

Uses

- helps prevent sunburn
- if used as directed with other sun protection measures (see Directions), decreases the risk of skin cancer and early skin aging casued by the sun

Warnings

For external use only

Do not use

• on damaged or broken skin

When using this product

• keep out of eyes. Rinse with water to remove.

Stop use and ask a doctor if

• rash occurs

Keep out of reach of children.

If swallowed, get medical help or contact a Poison Control Center right away.

Directions

- apply liberally 15 minutes before sun exposure

- reapply:

• after 80 minutes of swimming or sweating

• immediately after towel drying

• at least every 2 hours

- children under 6 months of age: Ask a doctor

- Sun Protection Measures. Spending time in the sun increases your risk of skin cancer and early skin aging. To decrease this risk, regularly use a sunscreen with a Broad Spectrum SPF value of 15 or higher and other sun protection measures including:

• limit time in the sun, especially from 10 a.m.-2 p.m.

• wear long-sleeved shirts, pants, hats, and sunglasses

Other information

- protect the product in this container from excessive heat and direct sun
- may stain or damage some fabrics, materials or surfaces

Inactive ingredients

Water, C12-15 Alkyl Benzoate, Neopentyl Glycol Diheptanoate, Propylene Glycol, Tridecyl Salicylate, Cyclopentasiloxane, Cetyl PEG/PPG-10/1 Dimethicone, PEG-12 Dimethicone Crosspolymer, Triethoxycaprylylsilane, Aloe Barbadensis Leaf Juice, Ethylhexyl Palmitate, Caprylyl Glycol, Phexoethanol, Hexylene Glycol, Sodium Chloride.